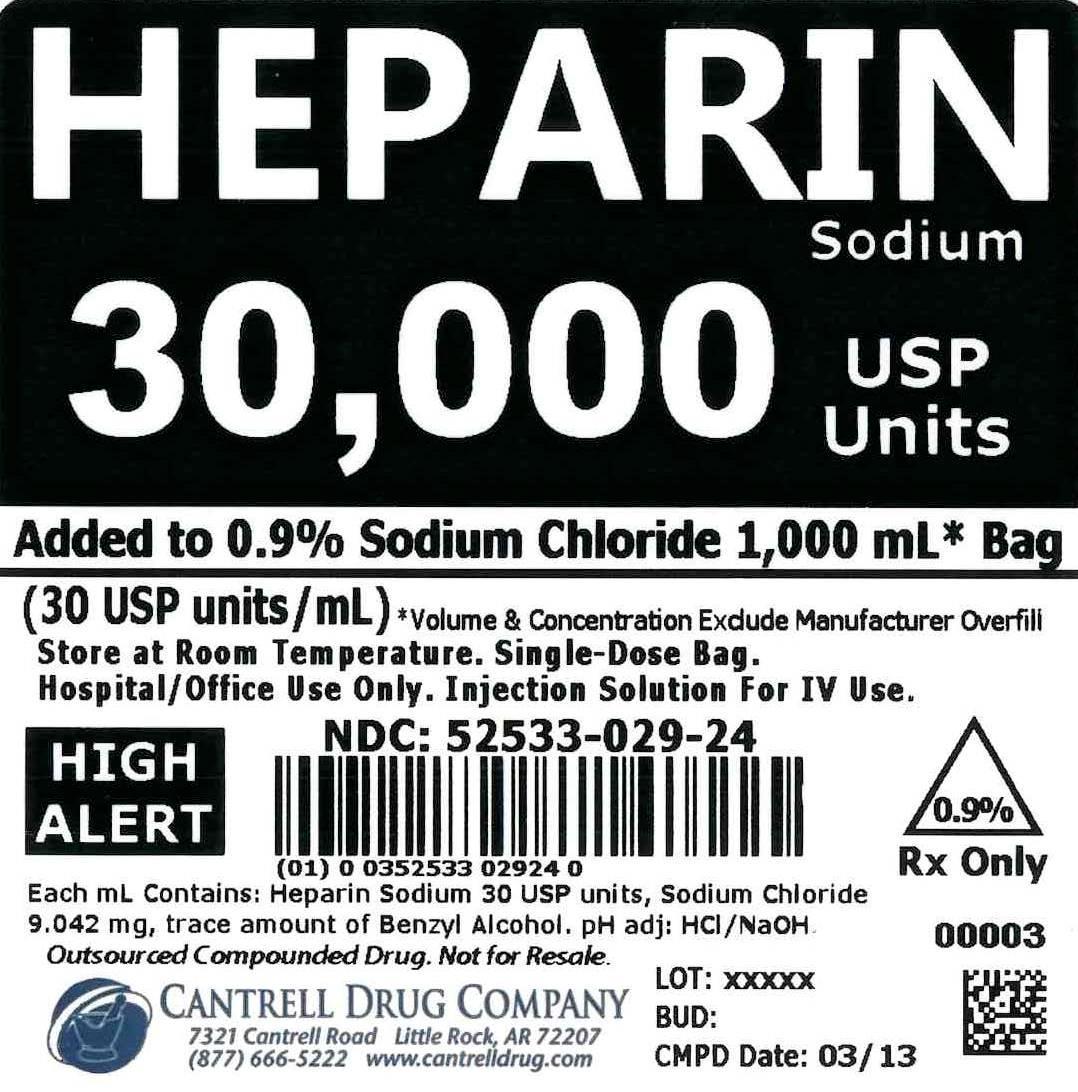 DRUG LABEL: Heparin Sodium
NDC: 52533-029 | Form: INJECTION, SOLUTION
Manufacturer: Cantrell Drug Company
Category: prescription | Type: HUMAN PRESCRIPTION DRUG LABEL
Date: 20141224

ACTIVE INGREDIENTS: Heparin Sodium 30 [USP'U]/1 mL
INACTIVE INGREDIENTS: Sodium Chloride 9 mg/1 mL; BENZYL ALCOHOL; Water

Heparin Sodium 30,000 USP Units Added to 0.9% Sodium Chloride 1,000 mL Bag